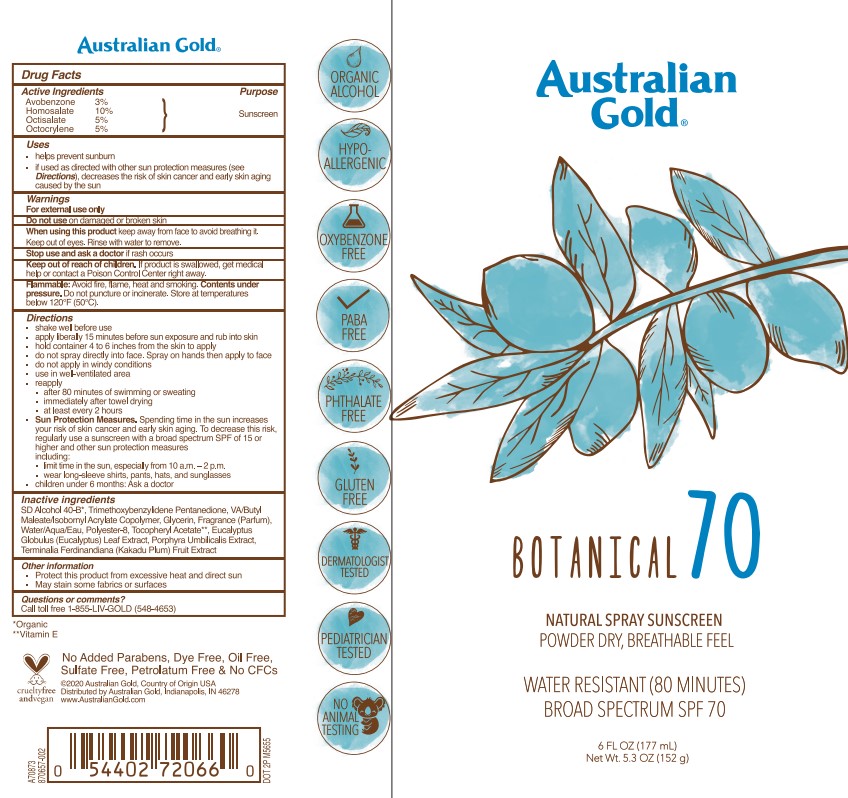 DRUG LABEL: Australian Gold
NDC: 13630-0191 | Form: SPRAY
Manufacturer: Prime Packaging, Inc.
Category: otc | Type: HUMAN OTC DRUG LABEL
Date: 20211115

ACTIVE INGREDIENTS: AVOBENZONE 25.6 mg/1 mL; HOMOSALATE 85.4 mg/1 mL; OCTISALATE 42.7 mg/1 mL; OCTOCRYLENE 42.7 mg/1 mL
INACTIVE INGREDIENTS: EUCALYPTUS GLOBULUS LEAF; WATER; .ALPHA.-TOCOPHEROL ACETATE; ISOBORNYL ACRYLATE; GLYCERIN; ALCOHOL; POLYESTER-8 (1400 MW, CYANODIPHENYLPROPENOYL CAPPED); KAKADU PLUM; PORPHYRA UMBILICALIS; TRIMETHOXYBENZYLIDENE PENTANEDIONE

AUSTRALIAN GOLD BOTANICAL 70 NATURAL SPRAY SUNSCREEN

Active Ingredients

Avobenzone 3%

Homosalate 10%

Octisalate 5%

Octocrylene 5%

Purpose

Sunscreen

Uses

- he lps prevent sunburn
- if used as directed with other sun protection measures (see Directions), decreases the risk of skin cancer and early skin aging caused by the sun

Warnings

For externa l use on ly

Do not use on damaged or broken skin

When using this product keep away from face to avoid breathing it. Keep out of eyes. Rinse with water to remove.

Stop use and ask a doctor if rash occurs

Keep out of reach of children. If product is swa llowed, get medica l help or contact a Poison Contro l Center right away.

F lammab le: Avoid fire, f lame heat and smoking. Contents under pressure. Do not puncture or incinerate. Store at temperatures below 120°F (50°C).

Directions

- shake well before use
- apply liberaly 15 minutes before sun exposure and rub into skin
- hold container 4 to 6 inches from the skin to apply
- do not spray directly Into face. Spray on hands then apply to face
- do not apply in windy conditions
- use in a well-ventilated area
- reapply:
- after 80 minutes of swimming or sweating
- immediately after towel drying
- at least every 2 hours
- Sun Protection Measures: Spending time in the sun increases your risk of skin cancer and early skin aging. To decrease this risk, regularly use a sunscreen with a broad spectrum SPF of 15 or higher and other sun protection measures including:
- limit time in the sun, especially from 10 a.m. – 2 p.m.
- wear long-sleeve shirts, pants, hats, and sunglasses
- children under 6 months: Ask a doctor

Inactive ingredients

SD Alcohol 40-B, Trimethoxybenzylidene Pentanedione, VA/Butyl Maleate/Isobornyl Acrylate Copolymer, Glycerin, Fragrance, Water, Polyester-8, Tocopheryl Acetate, Eucalyptus Globulus (Eucalyptus) Leaf Extract, Porphyra Umbilicalis Extract, Terminalia Ferdinandiana (Kakadu Plum) Fruit Extract

Other information

- Protect this product from excessive heat and direct sun
- May stain some fabrics or surfaces

Questions or comments?

Call toll free 1-885-LIV-GOLD (548-4653)